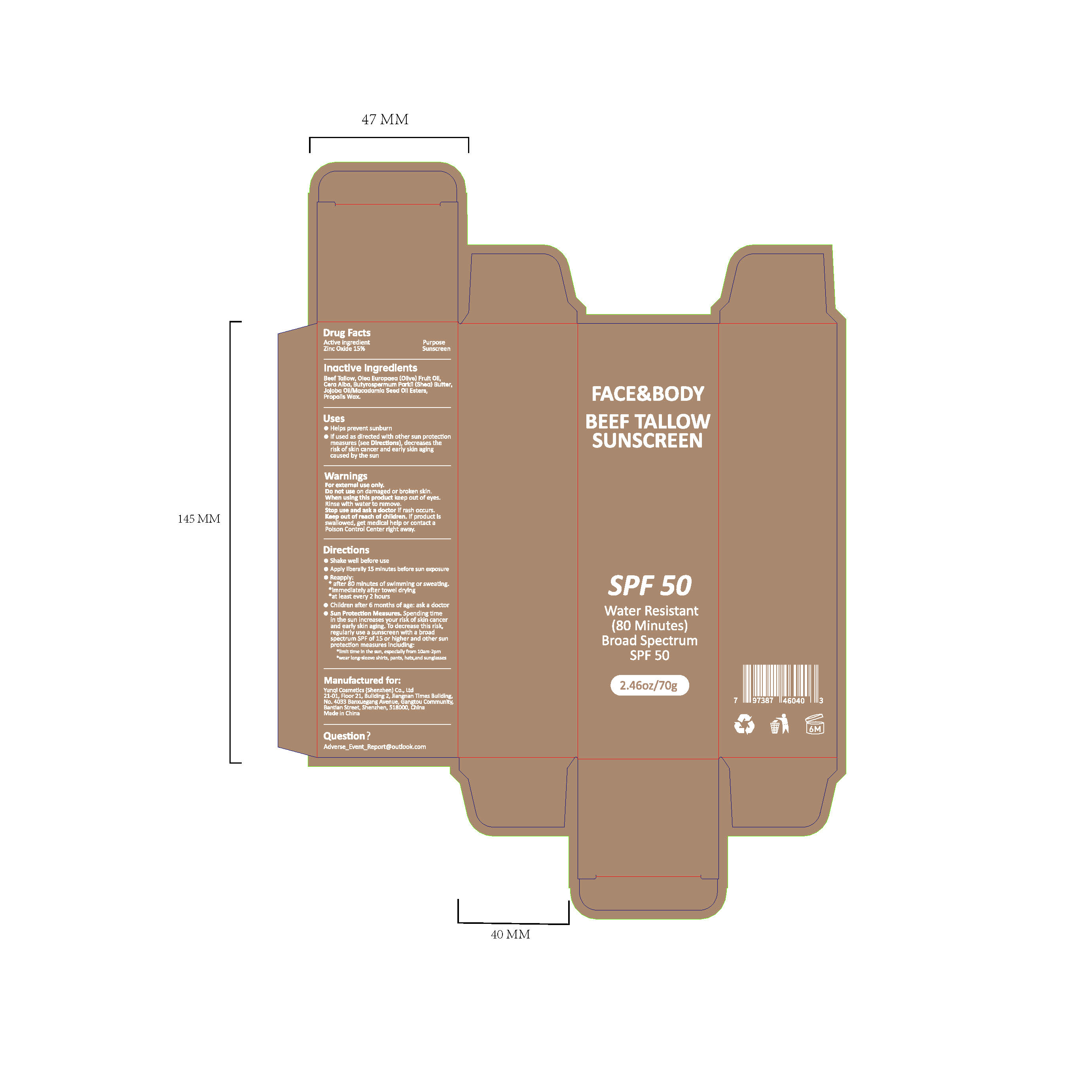 DRUG LABEL: BEEF TALLOW SUNSCREEN
NDC: 84763-005 | Form: CREAM
Manufacturer: Yunqi Cosmetics (Shenzhen) Co., Ltd
Category: otc | Type: HUMAN OTC DRUG LABEL
Date: 20250424

ACTIVE INGREDIENTS: ZINC OXIDE 0.15 g/1 g
INACTIVE INGREDIENTS: JOJOBA OIL, RANDOMIZED; PROPOLIS WAX; BUTYROSPERMUM PARKII (SHEA) BUTTER; WHITE WAX; BEEF TALLOW; OLEA EUROPAEA (OLIVE) FRUIT OIL

BEEF TALLOW SUNSCREEN

ACTIVE INGREDIENT

Zinc Oxide 15%

PURPOSE

Sunscreen

INDICATIONS AND USAGE

Helps prevent sunburn
If used as directed wlth other sun protectlonmeasures (see plrectlons,decreases therisk of skin cancer and early skin agingcaused by the sun

WARNINGS

For extemal use only.

When using thls product keep out of eves.
Rinse with water to remove.

Do not use on damaped or broken skin.

Stop use and ask a soctor lf rash occurs.

KEEP OUT OF REACH OF CHILDREN

Keep out of reach of chikren. if product lsswallowed, get medlcal help or contact a Polson control center right away

DOSAGE AND ADMINISTRATION

Shake well before use
Apply llberally 15 mlnutes before sun exposure
Reapply:
after 80 minutes of swlmming or sweating.
lmmedlately after towel dryingat least every 2 hours
Children after 6 months of age: ask a doctor
Sun Protection Measures. pending timein the sun inereases your risk of skin cancerand early skin aging. To decrease this ri5k.regularly use a sunscreen with a broadspectrum SPF of 15 or higher and other sunprotection measures including:
limit tme in the sun,essecllly fror 10am-2pm
wear long seeve shirts, pants, hats,and sunglasses

INACTIVE INGREDIENT

Beef Tallow
Olea Europaea (Olive) Fruit Oil
Cera Alba
Butyrospermum Parkii (Shea) Butter
Jojoba Oil/Macadamia Seed Oil Esters
Propolis Wax